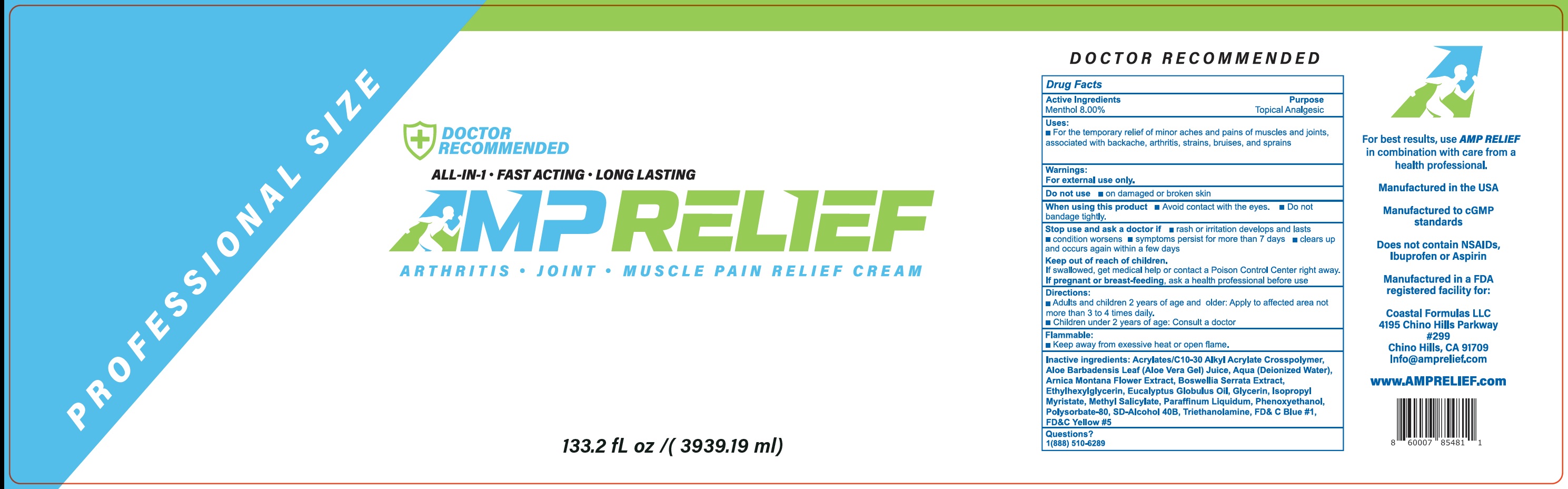 DRUG LABEL: AMP RELIEF Pain Relief Cream
NDC: 82560-283 | Form: CREAM
Manufacturer: COASTAL FORMULAS LLC
Category: otc | Type: HUMAN OTC DRUG LABEL
Date: 20231111

ACTIVE INGREDIENTS: MENTHOL 80 mg/1 mL
INACTIVE INGREDIENTS: ALOE VERA LEAF; WATER; ARNICA MONTANA FLOWER; INDIAN FRANKINCENSE; ETHYLHEXYLGLYCERIN; EUCALYPTUS OIL; GLYCERIN; ISOPROPYL MYRISTATE; METHYL SALICYLATE; MINERAL OIL; PHENOXYETHANOL; POLYSORBATE 80; TROLAMINE; FD&C BLUE NO. 1; FD&C YELLOW NO. 5

AMP RELIEF Pain Relief Cream

Active Ingredients

Menthol 8.00%

Purpose

Topical Analgesic

Uses:

- For the temporary relief of minor aches and pains of muscles and joints, associated with backache, arthritis, strains, bruises, and sprains

Warnings:

For external use only.

Do not use

- on damaged or broken skin

When using this product

- Avoid contact with the eyes.
- Do not bandage tightly.

Stop use and ask a doctor if

- rash or irritation develops and lasts
- condition worsens
- sysmptoms persist for more than 7 days
- clears up and occurs again within a few days

Keep out of reach of children.

If swallowed, get medical help or contact a Poison Control Center right away.

If pregnant or breast-feeding,

ask a health professional before use

Directions:

- Adults and children 2 years of age and older: Apply to affected area not more than 3 to 4 times daily.
- Children under 2 years of age: Consult a doctor

Flammable:

- Keep away from exessive heat or open flame.

Inactive ingredients:

Acrylates/C10-30 Alkyl Acrylate Crosspolymer, Aloe Barbadensis Leaf (Aloe Vera Gel) Juice, Aqua (Deionized Water), Arnica Montana Flower Extract, Boswellia Serrata Extract, Ethylhexylglycerin, Eucalyptus Globulus Oil, Glycerin, Isopropyl Myristate, Methyl Salicylate, Paraffinum Liquidum, Phenoxyethanol, Polysorbate-80, SD-Alcohol 40B, Triethanolamine, FD& C Blue #1, FD&C Yellow #5

Questions?

1(888) 510-6289